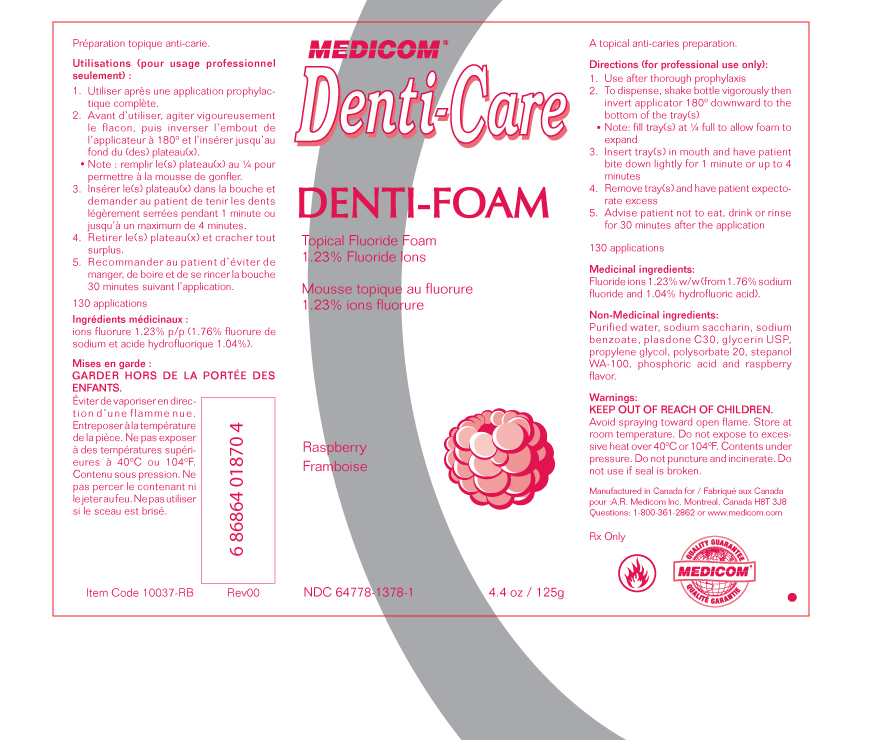 DRUG LABEL: Denti-Care
NDC: 64778-1378 | Form: AEROSOL, FOAM
Manufacturer: AR Medicom Inc
Category: prescription | Type: HUMAN PRESCRIPTION DRUG LABEL
Date: 20110209

ACTIVE INGREDIENTS: sodium fluoride .0176 g/1 g; HYDROFLUORIC ACID 0.010 g/1 g

Denti-Care Denti-Foam Topical Fluoride Foam Raspberry 1.23 % Fluoride Ions

DESCRIPTION

Denti-Care

Denti-Foam

Topical Fluoride Foam Raspberry

1.23 % Fluoride Ions

4.4 oz / 125 g

NDC 64778-1378-1

DOSAGE AND ADMINISTRATION

A topical anti-caries preparation

Directions (for professional use only):

1. Use after thorough prophylaxis

2. To dispense, shake bottle vigorously then invert applicator 180 degrees downward to the bottom of the tray(s)

Note: fill tray(s) at one quarter full to allow foam to expand

3. Insert tray(s) in mouth and have patient bite down lightly for 1 minute or up to 4 minutes

4. Remove tray(s) and have patient expectorate excess

5. Advise patient not to eat, drink or rinse for 30 minutes after the application

130 applications

Medicinal ingredients:

Fluoride ions 1.23 % w/w (from 1.76 % sodium fluoride and 1.04% hydrofluoric acid)

INACTIVE INGREDIENT

Non-Medicinal ingredients: sodium saccharin, sodium benzoate, plasdone C30, glycerin USP, propylene glycol, polysorbate 20, stepanol WA 100, phosphoric acid, purified water, raspberry flavor

Warnings: KEEP OUT OF REACH OF CHILDREN

Avoid spraying toward open flame. Store at room temperature. Do not expose to excessive heat over 40 degrees C or 104 degrees F. Contents under pressure. Do not puncture and incinerate.

Do not use if seal is broken.

Rx Only

Manufactured in Canada for
AR Medicom Inc
Montreal, Canada, H8T 3J8
Questions 1-800-361-2862 or www.medicom.com
UPC 686864018704
Item code 10037-RB
Rev 00